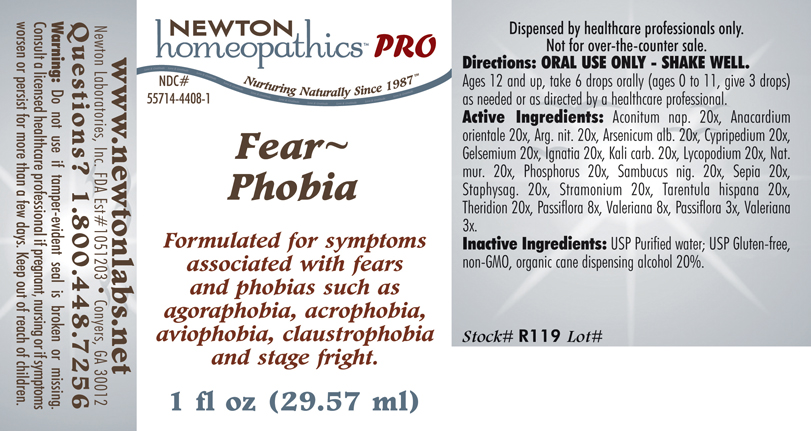 DRUG LABEL: Fear Phobia 
NDC: 55714-4408 | Form: LIQUID
Manufacturer: Newton Laboratories, Inc.
Category: homeopathic | Type: HUMAN PRESCRIPTION DRUG LABEL
Date: 20110601

ACTIVE INGREDIENTS: Aconitum Napellus 20 [hp_X]/1 mL; Semecarpus Anacardium Juice 20 [hp_X]/1 mL; Silver Nitrate 20 [hp_X]/1 mL; Arsenic Trioxide 20 [hp_X]/1 mL; Cypripedium Parvifolum Root 20 [hp_X]/1 mL; Gelsemium Sempervirens Root 20 [hp_X]/1 mL; Strychnos Ignatii Seed 20 [hp_X]/1 mL; Potassium Carbonate 20 [hp_X]/1 mL; Lycopodium Clavatum Spore 20 [hp_X]/1 mL; Sodium Chloride 20 [hp_X]/1 mL; Phosphorus 20 [hp_X]/1 mL; Sambucus Nigra Flowering Top 20 [hp_X]/1 mL; Sepia Officinalis Juice 20 [hp_X]/1 mL; Delphinium Staphisagria Seed 20 [hp_X]/1 mL; Datura Stramonium 20 [hp_X]/1 mL; Lycosa Tarantula 20 [hp_X]/1 mL; Theridion Curassavicum 20 [hp_X]/1 mL; Passiflora Incarnata Flowering Top 8 [hp_X]/1 mL; Valerian 8 [hp_X]/1 mL
INACTIVE INGREDIENTS: Alcohol

Fear Phobia

INDICATIONS & USAGE SECTION

Fear~Phobia Formulated for symptoms associated with fears and phobias such as agoraphobia, acrophobia, aviophobia, claustrophobia and stage fright.

DOSAGE & ADMINISTRATION SECTION

ORAL USE ONLY - SHAKE WELL. Ages 12 and up, take 6 drops orally (ages 0 to 11, give 3 drops) as needed or as directed by a healthcare professional.

ACTIVE INGREDIENT SECTION

Aconitum nap. 20x, Anacardium orientale 20x, Arg. nit. 20x, Arsenicum alb. 20x, Cypripedium 20x,Gelsemium 20x, Ignatia 20x, Kali carb. 20x, Lycopodium 20x, Nat.mur. 20x, Phosphorus 20x, Sambucus nig. 20x, Sepia 20x, Staphysag. 20x, Stramonium 20x, Tarentula hispana 20x, Theridion 20x, Passiflora 8x, Valeriana 8x, Passiflora 3x, Valeriana 3x.

PURPOSE SECTION

Formulated for symptoms associated with fears and phobias such as agoraphobia, acrophobia, aviophobia, claustrophobia and stage fright.

INACTIVE INGREDIENT SECTION

Inactive Ingredients: USP Purified Water; USP Gluten-free, non-GMO, organic cane dispensing alcohol 20%.

QUESTIONS? SECTION

www.newtonlabs.net Newton Laboratories, Inc. FDA Est # 1051203 - Conyers, GA 30012
Questions? 1.800.448.7256

WARNINGS SECTION

Warning: Do not use if tamper - evident seal is broken or missing. Consult a licensed healthcare professional if pregnant, nursing or if symptoms worsen or persist for more than a few days. Keep out of reach of children.

PREGNANCY OR BREAST FEEDING SECTION

Consult a licensed healthcare professional if pregnant, nursing or if symptoms worsen or persist for more than a few days.

KEEP OUT OF REACH OF CHILDREN SECTION

Keep out of reach of children.